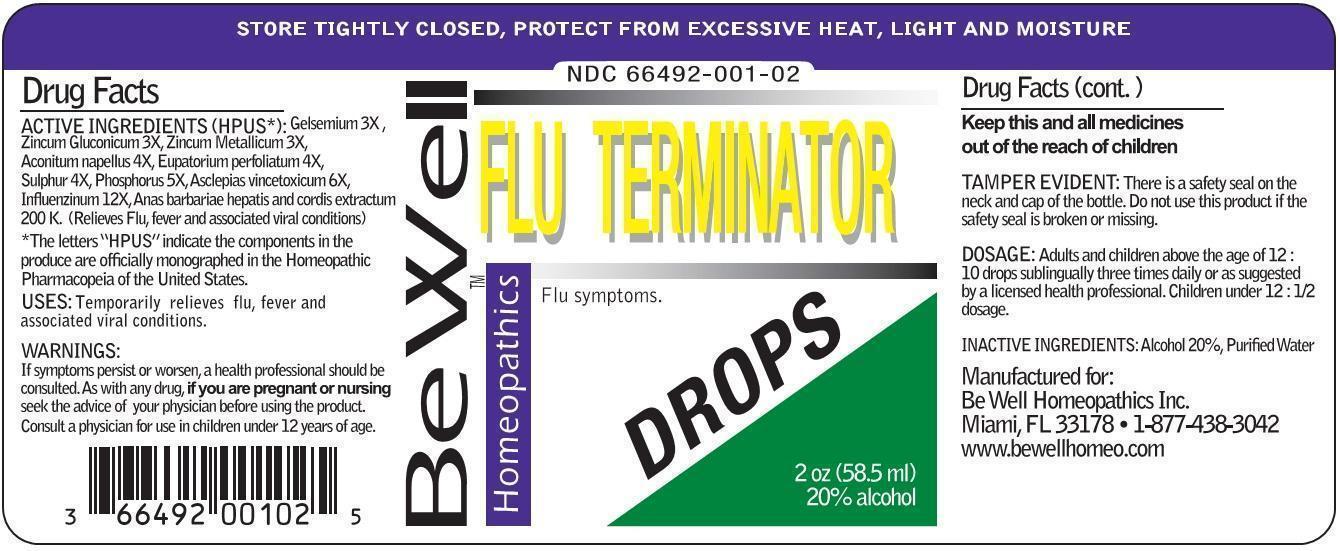 DRUG LABEL: FLU TERMINATOR DROPS
NDC: 66492-001 | Form: LIQUID
Manufacturer: Be Well Medical dba Richard Clement Nutrition y Be Well Homeopathics
Category: homeopathic | Type: HUMAN OTC DRUG LABEL
Date: 20211229

ACTIVE INGREDIENTS: GELSEMIUM SEMPERVIRENS ROOT 3 [hp_X]/1 mL; ZINC GLUCONATE 3 [hp_X]/1 mL; ZINC 3 [hp_X]/1 mL; ACONITUM NAPELLUS 4 [hp_X]/1 mL; EUPATORIUM PERFOLIATUM FLOWERING TOP 4 [hp_X]/1 mL; SULFUR 4 [hp_X]/1 mL; PHOSPHORUS 5 [hp_X]/1 mL; CYNANCHUM VINCETOXICUM ROOT 6 [hp_X]/1 mL; INFLUENZA A VIRUS 12 [hp_X]/1 mL; INFLUENZA B VIRUS 12 [hp_X]/1 mL; CAIRINA MOSCHATA HEART/LIVER AUTOLYSATE 200 [hp_C]/1 mL
INACTIVE INGREDIENTS: WATER; ALCOHOL

FLU TERMINATOR DROPS

ACTIVE INGREDIENT

ACTIVE INGREDIENTS (HPUS*): Gelsemium 3X, Zincum gluconicum 3X, Zincum metallicum 3X, Aconitum napellus 4X, Eupatorium perfoliatum 4X, Sulphur 4X, Phosphorus 5X, Asclepias vincetoxinum 6X, Influenzinum 12X, Anas barbarie hepatis et cordis extractum 200K. (Relieves flu, fever and associated viral conditions)

*The letters "HPUS" indicate the components in the produce are officially monographed in the Homeopathic Pharmacopeia of the United States.

INDICATIONS AND USAGE

USES: Temporarily relieves flu, fever and associated viral conditions.

WARNINGS:

If symptoms persist or worsen, a health professional should be consulted. As with any drug, if you are pregnant or nursing seek the advice of your physician before using the product. Consult a physician for use in children under 12 years of age.

KEEP OUT OF REACH OF CHILDREN

Keep this and all medicines out of the reach of children

OTHER SAFETY INFORMATION

TAMPER EVIDENT: There is a safety seal on the neck and cap of the bottle. Do not use this product if the safety seal is broken or missing.

STORE TIGHTLY CLOSED, PROTECT FROM EXCESSIVE HEAT, LIGHT AND MOISTURE

DOSAGE AND ADMINISTRATION

DOSAGE: Adults and children above the age of 12: 10 drops sublingually three times daily or as suggested by a licensed health professional. Children under 12: 1/2 dosage.

INACTIVE INGREDIENTS: Alcohol 20%, Purified Water.

QUESTIONS

Manufactured for:

Be Well Homeopathics Inc.

Miami, FL 33178

1-877-438-3042

www.bewellhomeo.com

PACKAGE LABEL

NDC 66492-001-02

Be Well HomeopathicsTM

FLU TERMINATOR DROPS

Flu symptoms.

2oz (58.5 ml)

20% Alcohol

PURPOSE

Flu symptoms.